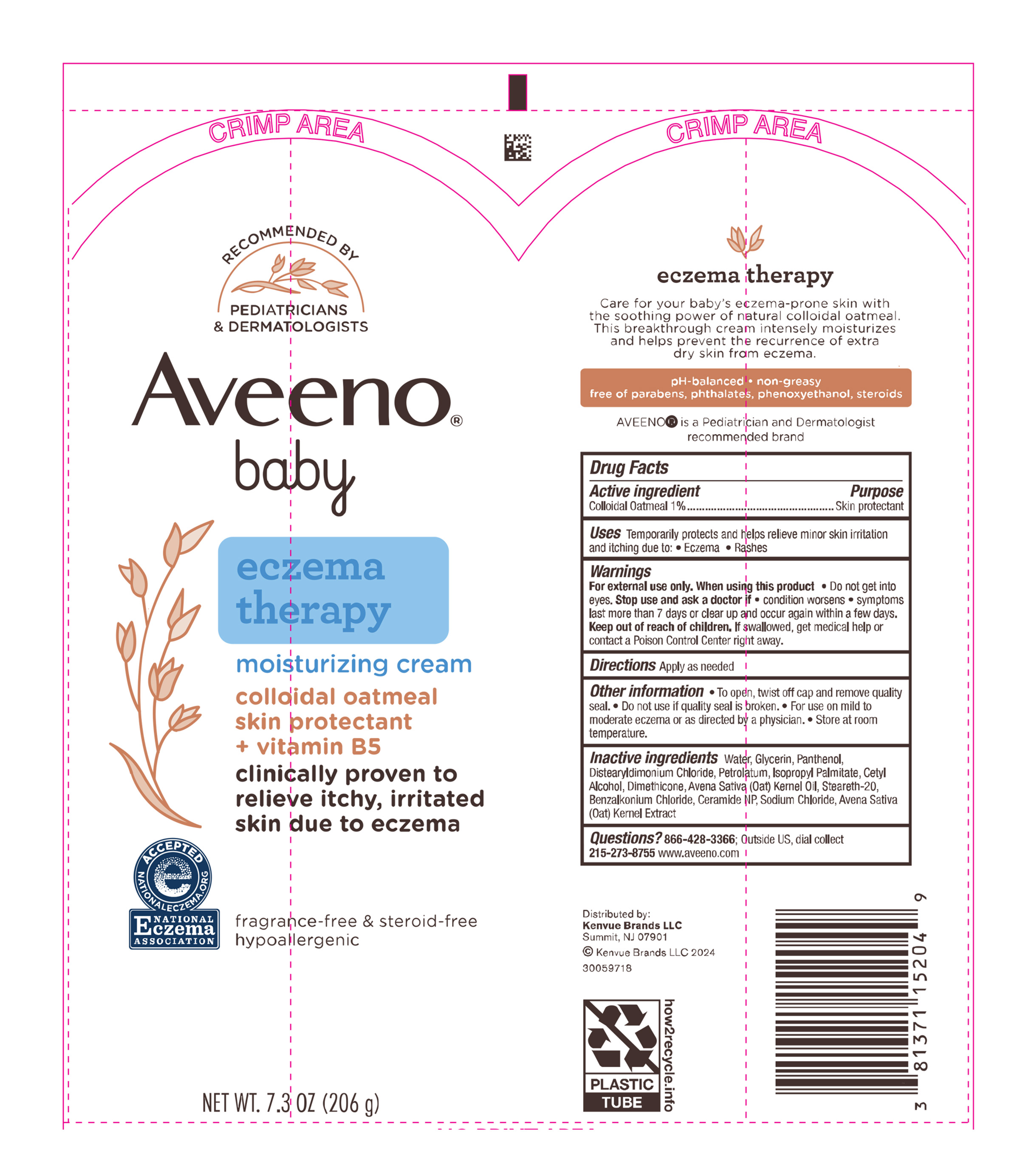 DRUG LABEL: Aveeno Baby Eczema Therapy Moisturizing
NDC: 69968-0404 | Form: CREAM
Manufacturer: Kenvue Brands LLC
Category: otc | Type: HUMAN OTC DRUG LABEL
Date: 20250926

ACTIVE INGREDIENTS: OATMEAL 10 mg/1 g
INACTIVE INGREDIENTS: WATER; GLYCERIN; PANTHENOL; DISTEARYLDIMONIUM CHLORIDE; ISOPROPYL PALMITATE; CETYL ALCOHOL; DIMETHICONE; OAT KERNEL OIL; STEARETH-20; BENZALKONIUM CHLORIDE; CERAMIDE NP; SODIUM CHLORIDE; OAT; PETROLATUM

Aveeno® baby eczema therapy moisturizing cream

Drug Facts

Active ingredient

Colloidal Oatmeal 1%

Purpose

Skin protectant

Uses

Temporarily protects and helps relieve minor skin irritation and itching due to:

- Eczema
- Rashes

Warnings

For external use only.

When using this product

- Do not get into eyes.

Stop use and ask a doctor if

- condition worsens
- symptoms last more than 7 days or clear up and occur again within a few days.

Keep out of reach of children. If swallowed, get medical help or contact a Poison Control Center right away.

Directions

Apply as needed

Other information

- To open, twist off cap and remove quality seal.
- Do not use if quality seal is broken.
- For use on mild to moderate eczema or as directed by a physician.
- Store at room temperature.

Inactive ingredients

Water, Glycerin, Panthenol, Distearyldimonium Chloride, Petrolatum, Isopropyl Palmitate, Cetyl Alcohol, Dimethicone, Avena Sativa (Oat) Kernel Oil, Steareth-20, Benzalkonium Chloride, Ceramide NP, Sodium Chloride, Avena Sativa (Oat) Kernel Extract

Questions?

866-428-3366; Outside US, dial collect 215-273-8755 www.aveeno.com

Distributed by:

Kenvue Brands LLC.

Summit, NJ 07901

PRINCIPAL DISPLAY PANEL - 206 g Tube Label

RECOMMENDED BY
PEDIATRICIANS
& DERMATOLOGISTS

Aveeno®

baby

eczema
therapy
moisturizing cream

colloidal oatmeal
skin protectant
+ vitamin B5
clinically proven to
relieve itchy, irritated
skin due to eczema

ACCEPTED

e

NATIONALECZEMA.ORG

NATIONAL

ECZEMA

ASSOCIATION

fragrance-free & steroid-free
hypoallergenic

NET WT. 7.3 OZ (206 g)